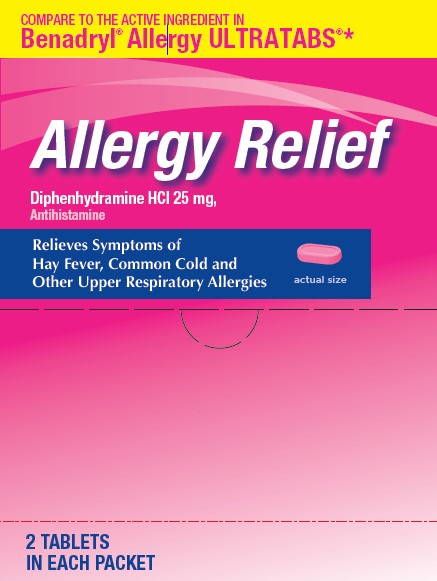 DRUG LABEL: Allergy Relief
NDC: 29485-9285 | Form: TABLET, FILM COATED
Manufacturer: Lil' Drug Store Products, Inc.
Category: otc | Type: HUMAN OTC DRUG LABEL
Date: 20240722

ACTIVE INGREDIENTS: DIPHENHYDRAMINE HYDROCHLORIDE 25 mg/1 1
INACTIVE INGREDIENTS: SILICON DIOXIDE; CARNAUBA WAX; MICROCRYSTALLINE CELLULOSE; D&C RED NO. 27; ANHYDROUS DIBASIC CALCIUM PHOSPHATE; TITANIUM DIOXIDE; LACTOSE, UNSPECIFIED FORM; CROSCARMELLOSE SODIUM; HYPROMELLOSE, UNSPECIFIED; POLYETHYLENE GLYCOL, UNSPECIFIED; POLYSORBATE 80; MAGNESIUM STEARATE

Allergy Relief Diphenhydramine HCl, 25 mg Antihistamine

Active Ingredient

Diphenhydramine HCl 25 mg

Purpose

Antihistamine

Uses

- temporarily relieves these symptoms due to hay fever or other upper respiratory allergies:
- runny nose
- sneezing
- itchy, watery eyes
- itching of the nose or throat
- temporarily relieves these symptoms due to the common cold
- runny nose
- sneezing

Warnings

Do not use

- to make a child sleepy
- with any other product containing diphenhydramine, even one used on skin

Ask a doctor before use if you have

- a breathing problem such as emphysema or chronic bronchitis
- glaucoma
- trouble urinating due to an enlarged prostate gland

Ask a doctor or pharmacist before use if you are

taking tranquilizers or sedatives.

When using this product

- marked drowsiness may occur
- avoid alcoholic drinks
- alcohol, sedatives and tranquilizers may increase drowsiness
- be careful when driving a motor vehicle or operating machinery
- excitability may occur, especially in children

If pregnant or breast-feeding,

ask a health professional before use.

Keep out of reach of children.

In case of overdose, get medical help or contact a Poison Control Center right away (1-800-222-1222).

Directions

- take every 4 to 6 hours, or as directed by a doctor
- do not take more than 6 doses in 24 hours

adults and children 12 years and over | take 1 to 2 tablets
children 6 to under 12 years | take 1 tablet
children under 6 years | do not use

Other Information

- each tablet may contain: calcium 25 mg
- store at room temperature 68°-77°F (20°-25°C)
- protect from light and moisture

Inactive Ingredients

carnauba wax [may contain] , colloidal silicon dioxide, croscarmellose sodium, D&C red #27, dicalcium phosphate , hypromellose, lactose , magnesium stearate, microcrystalline cellulose, polyethylene glycol, polysorbate 80 , titanium dioxide

Questions or Comments

call toll-free 800-351-2000 (M-F 8:00 AM-4:30 PM CST)

* This product is not manufactured or distributed by

JOHNSON & JOHNSON CONSUMER INC,

McNeil Consumer Healthcare Division,

distributor of Benadryl® Allergy ULTRATABS®

Distributed by:

Lil’ Drug Store Products, Inc.

Cedar Rapids, IA 52404

PACKAGE LABEL

COMPARE TO THE ACTIVE INGREDIENTS IN

Benadryl® Allergy ULTRATABS®

Allergy Relief

Diphenhydramine HCl 25 mg,

Antihistamine

Relieves Symptoms of

Hay Fever, Common Cold and [tablet image here]

Other Upper Respiratory Allergies actual size

2 TABLETS IN EACH PACKET